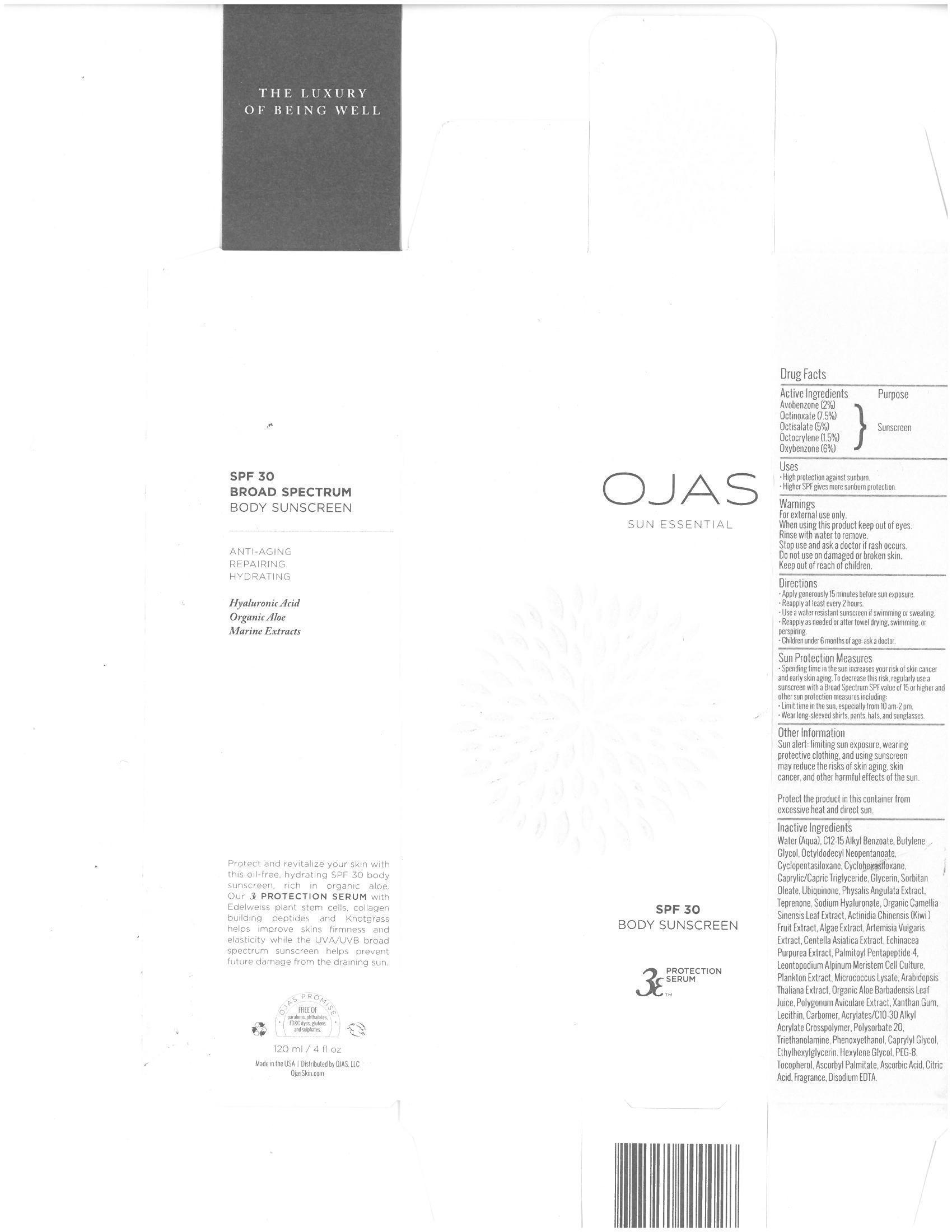 DRUG LABEL: SPF 30 Body Sunscreen
NDC: 70867-101 | Form: CREAM
Manufacturer: OJAS, LLC
Category: otc | Type: HUMAN OTC DRUG LABEL
Date: 20160726

ACTIVE INGREDIENTS: AVOBENZONE 20 mg/1 mL; OCTINOXATE 75 mg/1 mL; OCTISALATE 50 mg/1 mL; OCTOCRYLENE 15 mg/1 mL; OXYBENZONE 60 mg/1 mL
INACTIVE INGREDIENTS: WATER; ALKYL (C12-15) BENZOATE; BUTYLENE GLYCOL; OCTYLDODECYL NEOPENTANOATE; CYCLOMETHICONE 5; MEDIUM-CHAIN TRIGLYCERIDES; GLYCERIN; SORBITAN MONOOLEATE; UBIDECARENONE; PHYSALIS ANGULATA; TEPRENONE; HYALURONATE SODIUM; GREEN TEA LEAF; ACTINIDIA CHINENSIS ROOT; ARTEMISIA VULGARIS ROOT; CENTELLA ASIATICA; ECHINACEA PURPUREA; PALMITOYL PENTAPEPTIDE-4; LEONTOPODIUM ALPINUM FLOWER; ARABIDOPSIS THALIANA; ALOE VERA LEAF; POLYGONUM AVICULARE TOP; XANTHAN GUM; EGG PHOSPHOLIPIDS; CARBOMER COPOLYMER TYPE B (ALLYL PENTAERYTHRITOL CROSSLINKED); CARBOMER COPOLYMER TYPE A (ALLYL PENTAERYTHRITOL CROSSLINKED); POLYSORBATE 20; TROLAMINE; PHENOXYETHANOL; CAPRYLYL GLYCOL; ETHYLHEXYLGLYCERIN; HEXYLENE GLYCOL; POLYETHYLENE GLYCOL 400; TOCOPHEROL; ASCORBYL PALMITATE; ASCORBIC ACID; CITRIC ACID MONOHYDRATE; EDETATE DISODIUM

Active Ingredients:

Avobenzone - 2%

Octinoxate - 7.5%

Octisalate - 5%

Octocrylene - 1.5%

Oxybenzone - 6%

Purpose: Sunscreen

Uses:

- High protection against sunburn.
- Higher SPF gives more sunburn protection.

Warnings: For external use only.

When using this product keep out of eyes. Rinse with to remove.

Stop use ans ask a doctor if rash occurs.

Do not use on damaged or broken skin.

Keep out of reach of children.

Directions:

- Apply generously 15 minutes before sun exposure.
- Reapply at least every 2 hours.
- Use a water resistant sunscreen if swimming or sweating.
- Reapply as needed or after towel drying, swimming or perspiring.
- children under 6 months of age: ask a doctor.

STORAGE AND HANDLING

Protect the product in in this container from excessive heat and direct sun.

INACTIVE INGREDIENT

Inactive Ingredients: Water (Aqua), C12-15 Alkyl Benzoate, Butylene Glycol, Octyldodecyl Neopentanoate, Cyclopentasiloxane, Cyclohexaciloxane, Caprylic/Capric Triglyceride, Glycerin, Sorbitan Oleate, Ubiquinone, Physalis Angulata Extract, Teprenone, Sodium Hyaluronate, Organic Camellia Sinensis Leaf Extract, Actinidia Chinensis (Kiwi) Fruit Extract, Algae Extract, Artemisia Vulgaris Extract, Centella Asiatica Extract, Echinacea Purpurea Extract, Palmitoyl Pentapeptide-4, Leontopodium Alpinum Meristem Cell Culture, Plankton Extract, Micrococcus Lysate, Arabidopsis Thaliana Extract, Organic Aloe Barbadensis Leaf Juice, Polygonum Aviculare Extract, Xanthan Gum, Lecithin, Carbomer, Acrylates/C10-30 Alkyl Acrylate Crosspolymer, Polysorbate 20, Triethanolamine, Phenoxyethanol, Caprylyl Glycol, Ethylhexylglycerin, Hexylene Glycol, PEG-8, Tocopherol, Ascorbyl Palmitate, Ascorbic Acid, Citric Acid, Fragrance, Disodium EDTA.

PACKAGE LABEL

Made in USA

Distributed By OJAS, LLC

OjasSkin.com